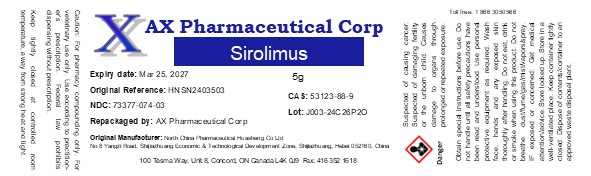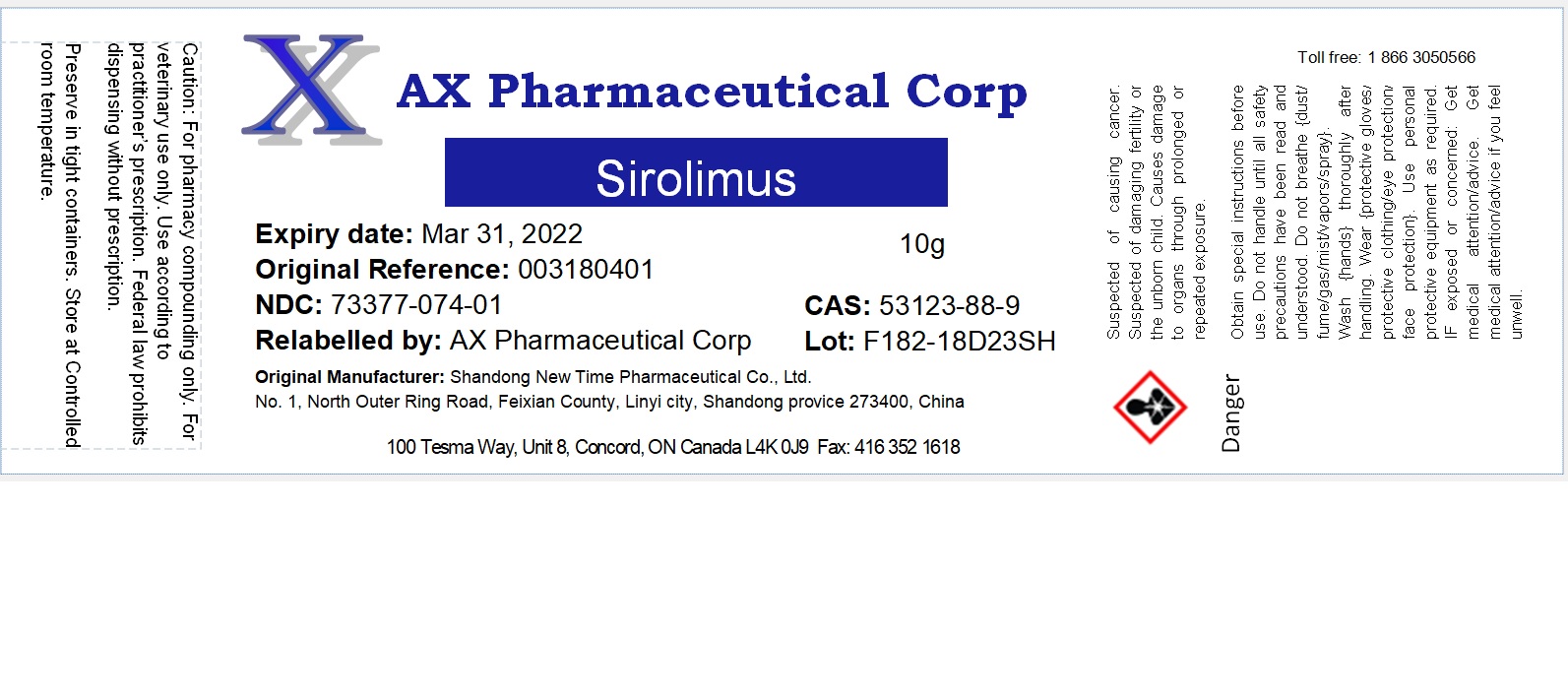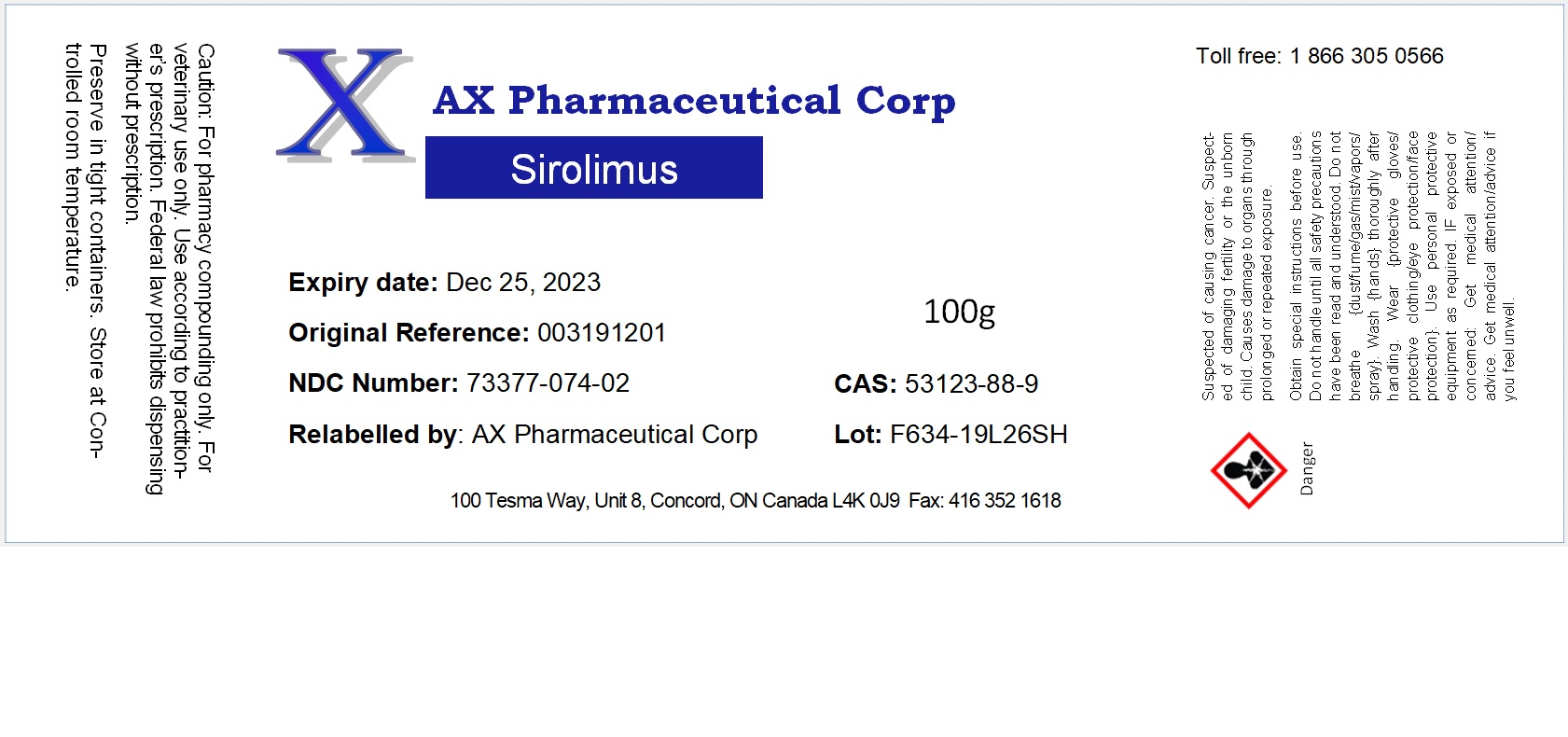 DRUG LABEL: Sirolimus
NDC: 73377-074 | Form: POWDER
Manufacturer: AX Pharmaceutical Corp
Category: other | Type: BULK INGREDIENT - ANIMAL DRUG
Date: 20250212

ACTIVE INGREDIENTS: SIROLIMUS 1 g/1 g

Sirolimus